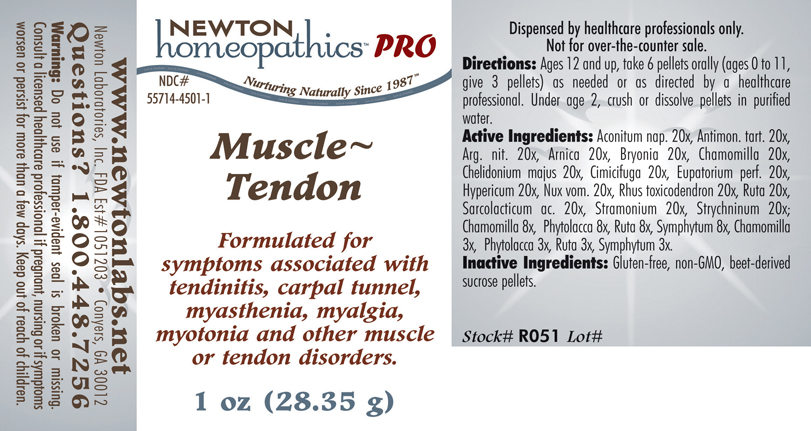 DRUG LABEL: Muscle - Tendon 
NDC: 55714-4501 | Form: PELLET
Manufacturer: Newton Laboratories, Inc.
Category: homeopathic | Type: HUMAN PRESCRIPTION DRUG LABEL
Date: 20110601

ACTIVE INGREDIENTS: Aconitum Napellus 20 [hp_X]/1 g; Antimony Potassium Tartrate 20 [hp_X]/1 g; Silver Nitrate 20 [hp_X]/1 g; Arnica Montana 20 [hp_X]/1 g; Bryonia Alba Root 20 [hp_X]/1 g; Matricaria Recutita 20 [hp_X]/1 g; Chelidonium Majus 20 [hp_X]/1 g; Black Cohosh 20 [hp_X]/1 g; Eupatorium Perfoliatum Flowering Top 20 [hp_X]/1 g; Hypericum Perforatum 20 [hp_X]/1 g; Strychnos Nux-vomica Seed 20 [hp_X]/1 g; Toxicodendron Pubescens Leaf 20 [hp_X]/1 g; Ruta Graveolens Flowering Top 20 [hp_X]/1 g; Lactic Acid, L- 20 [hp_X]/1 g; Datura Stramonium 20 [hp_X]/1 g; Strychnine 20 [hp_X]/1 g; Phytolacca Americana Root 8 [hp_X]/1 g; Comfrey Root 8 [hp_X]/1 g
INACTIVE INGREDIENTS: Sucrose

Muscle - Tendon

INDICATIONS & USAGE SECTION

Muscle - Tendon Formulated for symptoms associated with tendinitis, carpal tunnel, myasthenia, myalgia, myotonia and other muscle or tendon disorders.

DOSAGE & ADMINISTRATION SECTION

Directions: Ages 12 and up, take 6 pellets orally (ages 0 to 11, give 3 pellets) as needed or as directed by a healthcare professional. Under age 2, crush or dissolve pellets in purified water.

ACTIVE INGREDIENT SECTION

Aconitum nap. 20x, Antimon. tart. 20x, Arg. nit. 20x, Arnica 20x, Bryonia 20x, Chamomilla 20x, Chelidonium majus 20x, Cimicifuga 20x, Eupatorium perf. 20x, Hypericum 20x, Nux vom. 20x, Rhus toxicodendron 20x, Ruta 20x, Sarcolacticum ac. 20x, Stramonium 20x, Strychninum 20x, Chamomilla 8x, Phytolacca 8x, Ruta 8x, Symphytum 8x, Chamomilla 3x, Phytolacca 3x, Ruta 3x, Symphytum 3x.

PURPOSE SECTION

Formulated for symptoms associated with tendinitis, carpal tunnel, myasthenia, myalgia, myotonia and other muscle or tendon disorders.

INACTIVE INGREDIENT SECTION

Inactive Ingredients: Gluten-free, non-GMO, beet-derived sucrose pellets.

QUESTIONS? SECTION

www.newtonlabs.net Newton Laboratories, Inc. FDA Est # 1051203 - Conyers, GA 30012
Questions? 1.800.448.7256

WARNINGS SECTION

Warning: Do not use if tamper - evident seal is broken or missing. Consult a licensed healthcare professional if pregnant, nursing or if symptoms worsen or persist for more than a few days. Keep out of reach of children.

PREGNANCY OR BREAST FEEDING SECTION

Consult a licensed healthcare professional if pregnant, nursing or if symptoms worsen or persist for more than a few days.

KEEP OUT OF REACH OF CHILDREN SECTION

Keep out of reach of children.